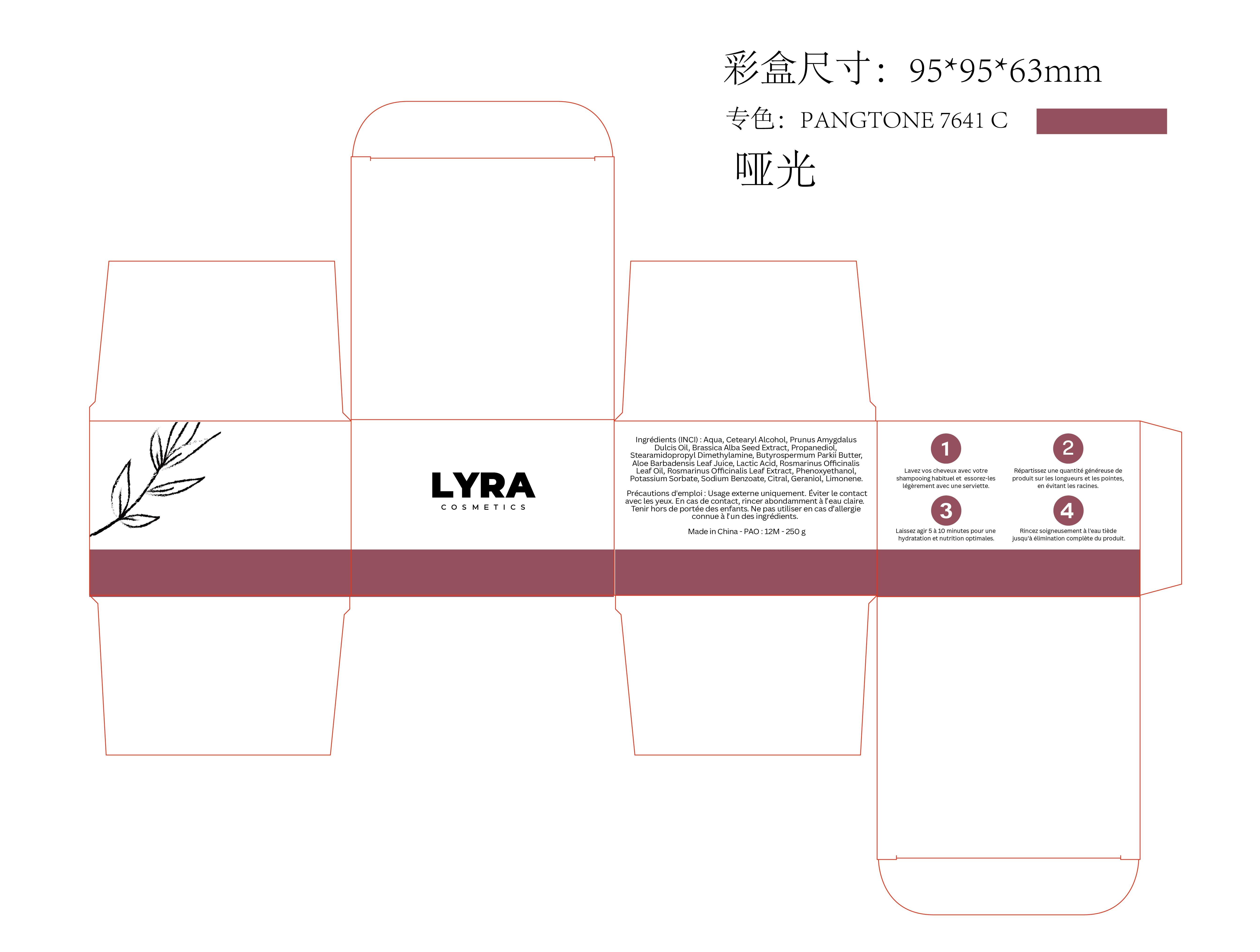 DRUG LABEL: LYRA Rosemary Hair Growth Cream
NDC: 85594-009 | Form: CREAM
Manufacturer: Dongguan Haiyi Cosmetics Co., Ltd.
Category: otc | Type: HUMAN OTC DRUG LABEL
Date: 20251118

ACTIVE INGREDIENTS: BRASSICA ALBA SPROUT 5 mg/250 g
INACTIVE INGREDIENTS: GERANIOL; STEARAMIDOPROPYL DIMETHYLAMINE; LACTIC ACID; CITRAL; ALOE BARBADENSIS LEAF JUICE; PRUNUS AMYGDALUS DULCIS (SWEET ALMOND) OIL; ROSMARINUS OFFICINALIS (ROSEMARY) LEAF OIL; BUTYROSPERMUM PARKII (SHEA) BUTTER; CETEARYL ALCOHOL; LIMONENE, (+/-)-; ROSMARINUS OFFICINALIS (ROSEMARY) LEAF POWDER; PROPANEDIOL; SODIUM BENZOATE; POTASSIUM SORBATE; AQUA; PHENOXYETHANOL

85594-009-00 LYRA Rosemary Hair Growth Cream

ACTIVE INGREDIENT

Brassica Alba Seed Extract

INACTIVE INGREDIENT

Aqua, Cetearyl Alcohol, Prunus AmygdalusDulcis Oil, Propanediol,StearamidopropylDimethylamine, Butyrospermum Parkii ButterAloe Barbadensis Leaf Juice, Lactic Acid, Rosmarinus OffcinalisLeaf Oil, Rosmarinus Offcinalis Leaf Extract, Phenoxyethanol,Potassium Sorbate, Sodium Benzoate, Citral, Geraniol, Limonene.

PURPOSE

Promotes blood circulation in the scalp, thereby stimulating hair follicle function.

WARNINGS

1).For external use only, avoid directcontact with eyes, lf you feel any
discomfort, stop using itand wash it with plenty of water. In severe cases,
pleaseseek medical attention in time.
2). Not allowed to be used ondamaged skin,

STOP USE

This product may cause allergic reactions in asmall number of people.
lf youexperience any discomfort,please stop using it immediately.

DO NOT USE

Not suitable for use by children, pregnantor breast feeding people.

KEEP OUT OF REACH OF CHILDREN

KEEP THE PRODUCT OUT OF REACH OF CHILDREN to

INDICATIONS AND USAGE

This product is intended for topical use on the scalp to help improve the appearance of thinning hair and support a healthy scalp environment. The cream is formulated with botanical extracts, including rosemary, to moisturize the scalp, enhance hair softness, and promote a visibly fuller and healthier look of the hair.

It is suitable for individuals experiencing dry scalp, reduced hair density, or dull-looking hair, and can be used as part of a daily scalp-care routine.
This product is a cosmetic and is not intended to diagnose, treat, cure, or prevent any disease.

DOSAGE AND ADMINISTRATION

take an appropriateamount,Use 2-3 times a week